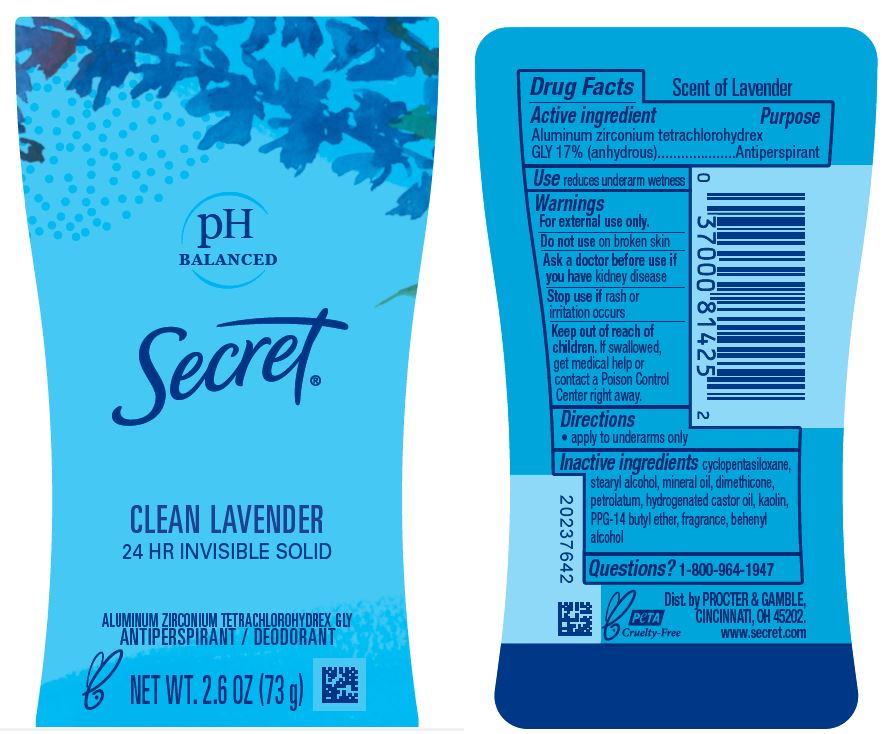 DRUG LABEL: Secret Clean Lavender Invisible
NDC: 69423-737 | Form: STICK
Manufacturer: The Procter & Gamble Manufacturing Company
Category: otc | Type: HUMAN OTC DRUG LABEL
Date: 20251231

ACTIVE INGREDIENTS: ALUMINUM ZIRCONIUM TETRACHLOROHYDREX GLY 17 g/100 g
INACTIVE INGREDIENTS: KAOLIN; PETROLATUM; MINERAL OIL; PPG-14 BUTYL ETHER; CYCLOMETHICONE 5; STEARYL ALCOHOL; DIMETHICONE; HYDROGENATED CASTOR OIL; DOCOSANOL

Secret® Clean Lavender nvisible Solid Antiperspirant/Deodorant

Drug Facts

Active ingredient

Aluminum zirconium tetrachlorohydrex Gly 17% (anhydrous)

Purpose

Antiperspirant

Use

reduces underarm wetness

Warnings

For external use only.

Do not use on broken skin

Ask a doctor before use if you have kidney disease

Stop use if rash or irritation occurs

Keep out of reach of children. If swallowed, get medical help or contact a Poison Control Center right away.

Directions

apply to underarms only

Inactive ingredients

cyclopentasiloxane, stearyl alcohol, mineral oil, dimethicone, petrolatum, hydrogenated castor oil, kaolin, PPG-14 butyl ether, fragrance, behenyl alcohol

Questions?

1-800-964-1947

Dist. by Procter & Gamble, Cincinnati, OH 45202.

PRINCIPAL DISPLAY PANEL - 73 g Canister Label

pH BALANCED

Secret®

CLEAN LAVENDER

24 HR INVISIBLE SOLID

Aluminum zirconium tetraachlorohydrex GLY
ANTIPERSPIRANT/DEODORANT

Net Wt. 2.6 OZ (73 g)